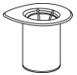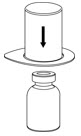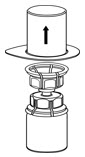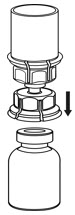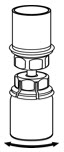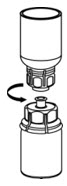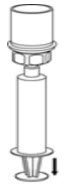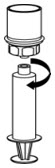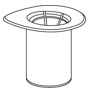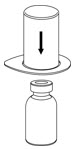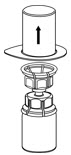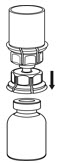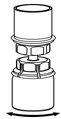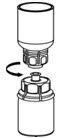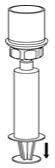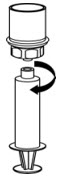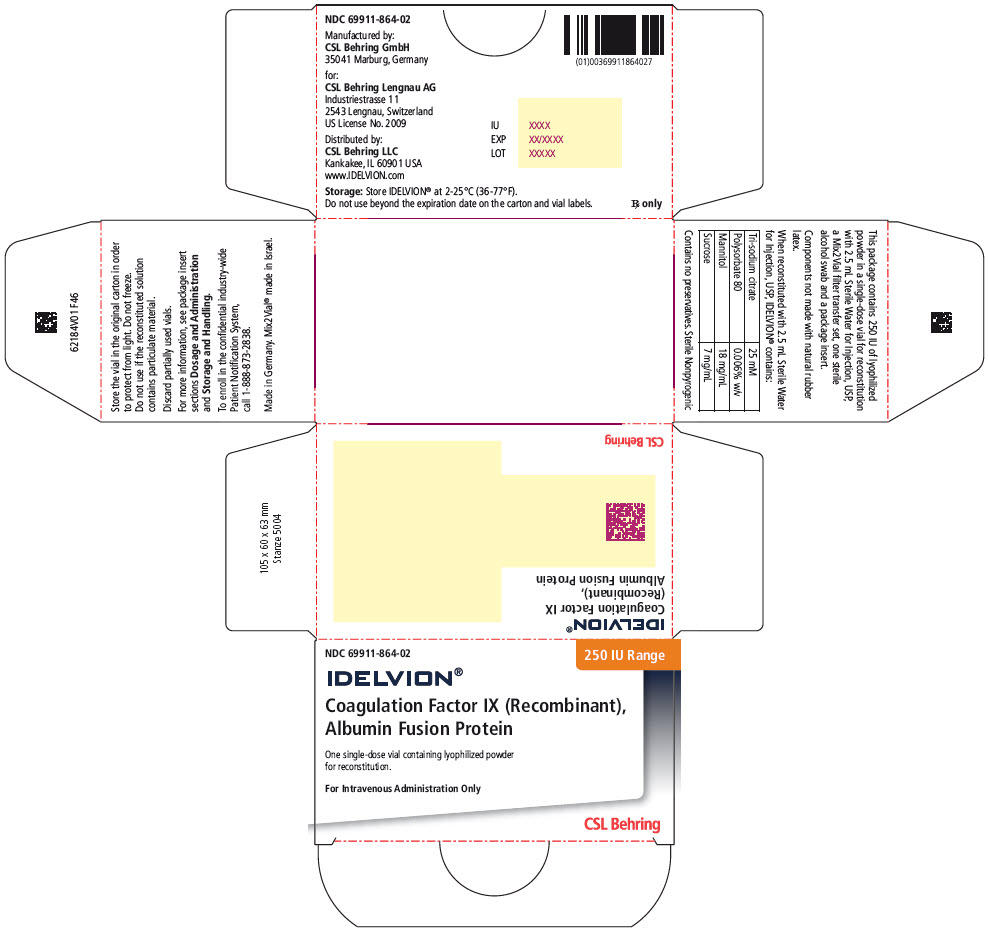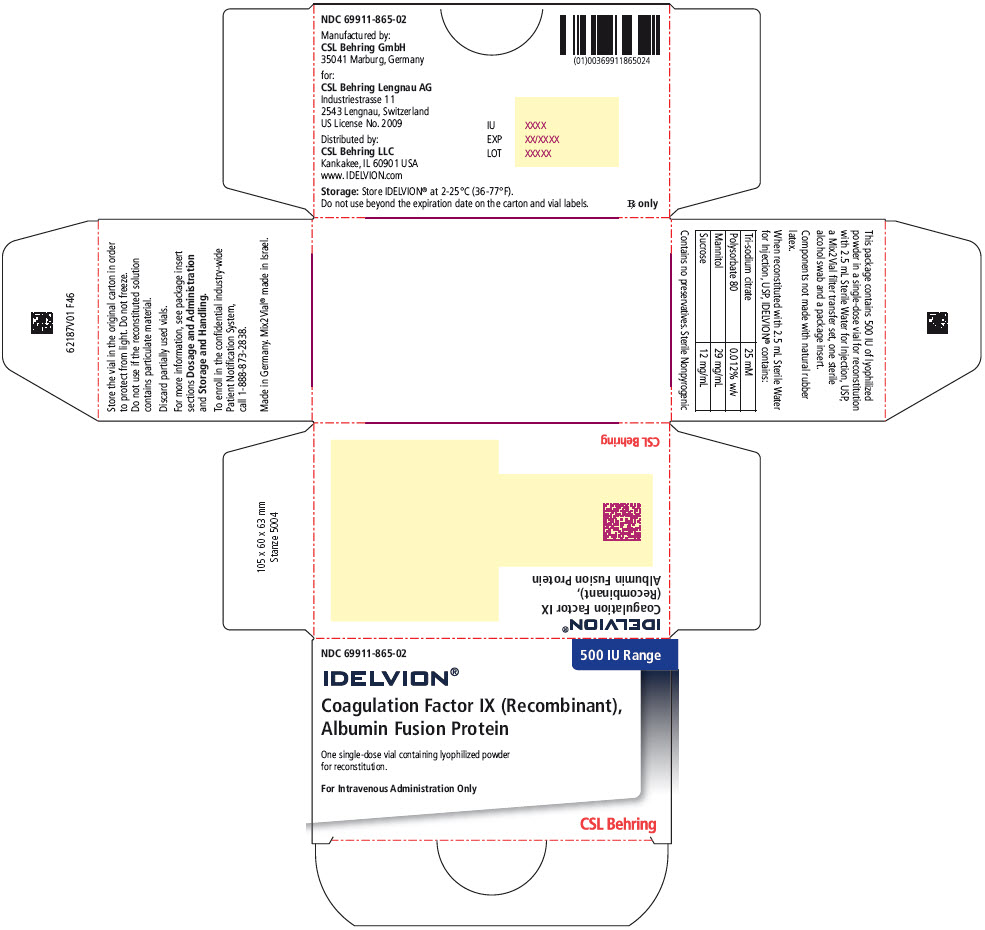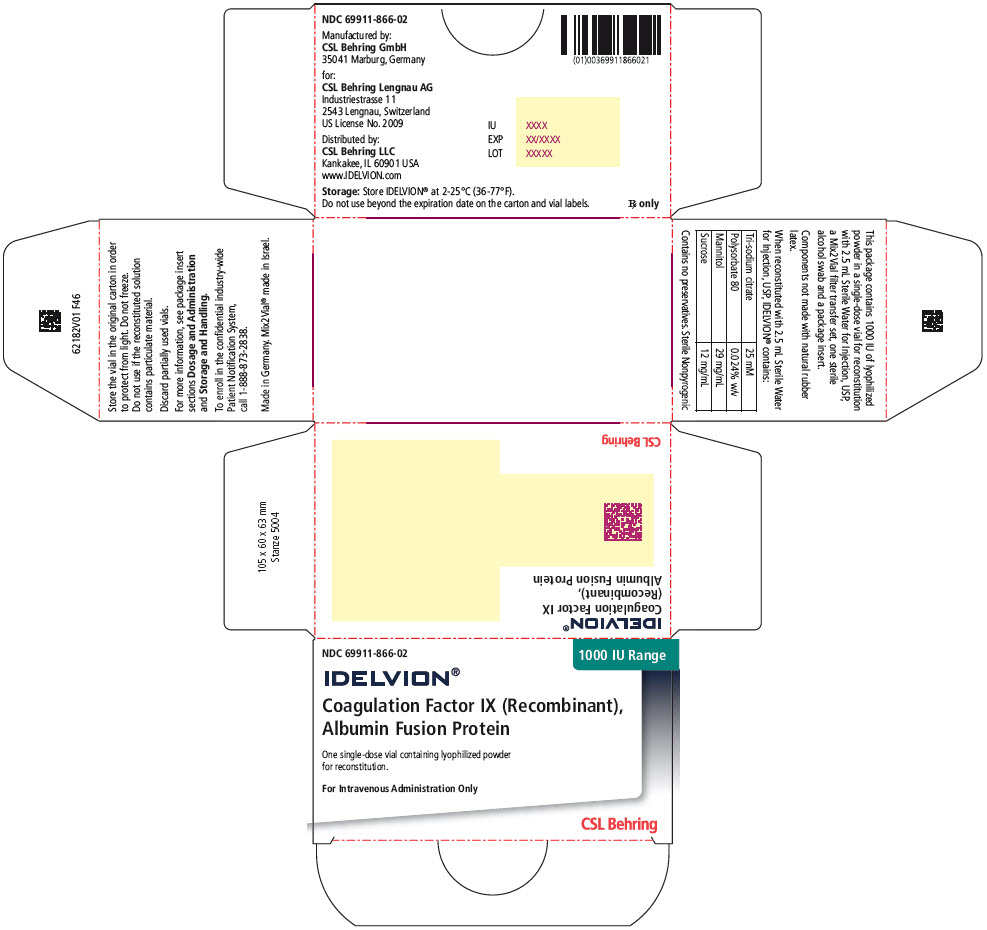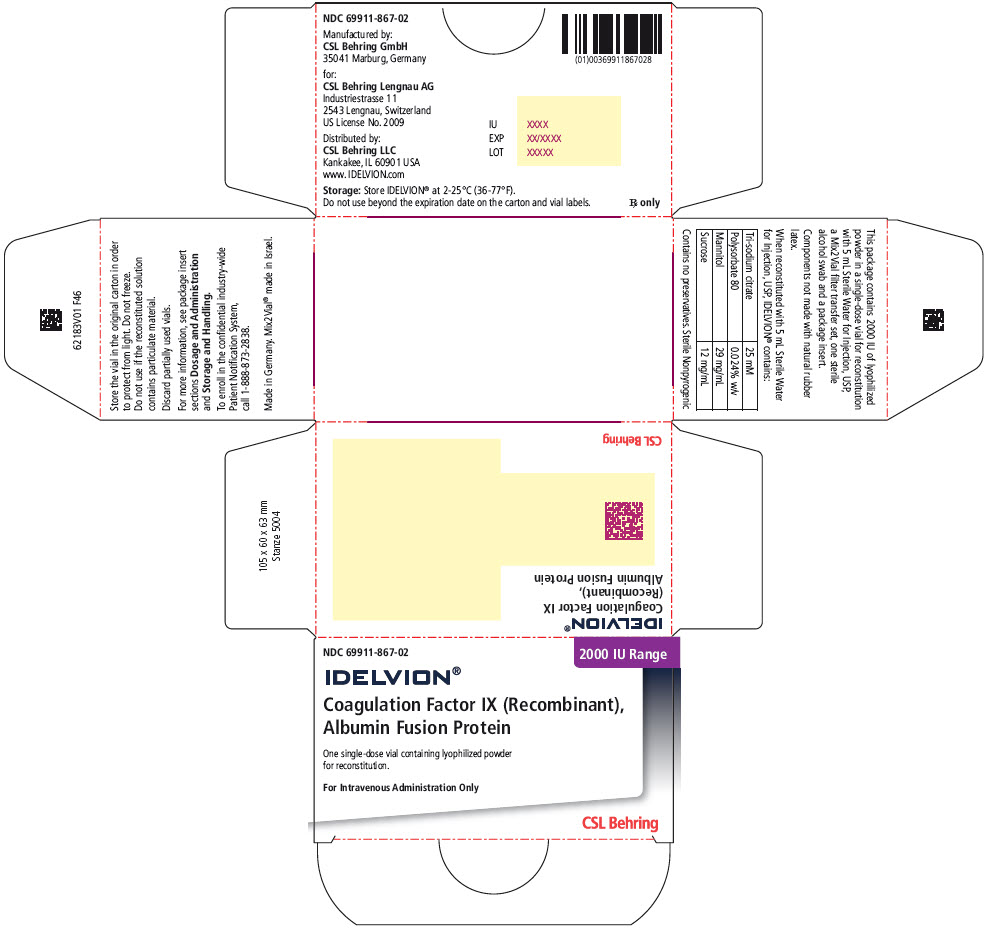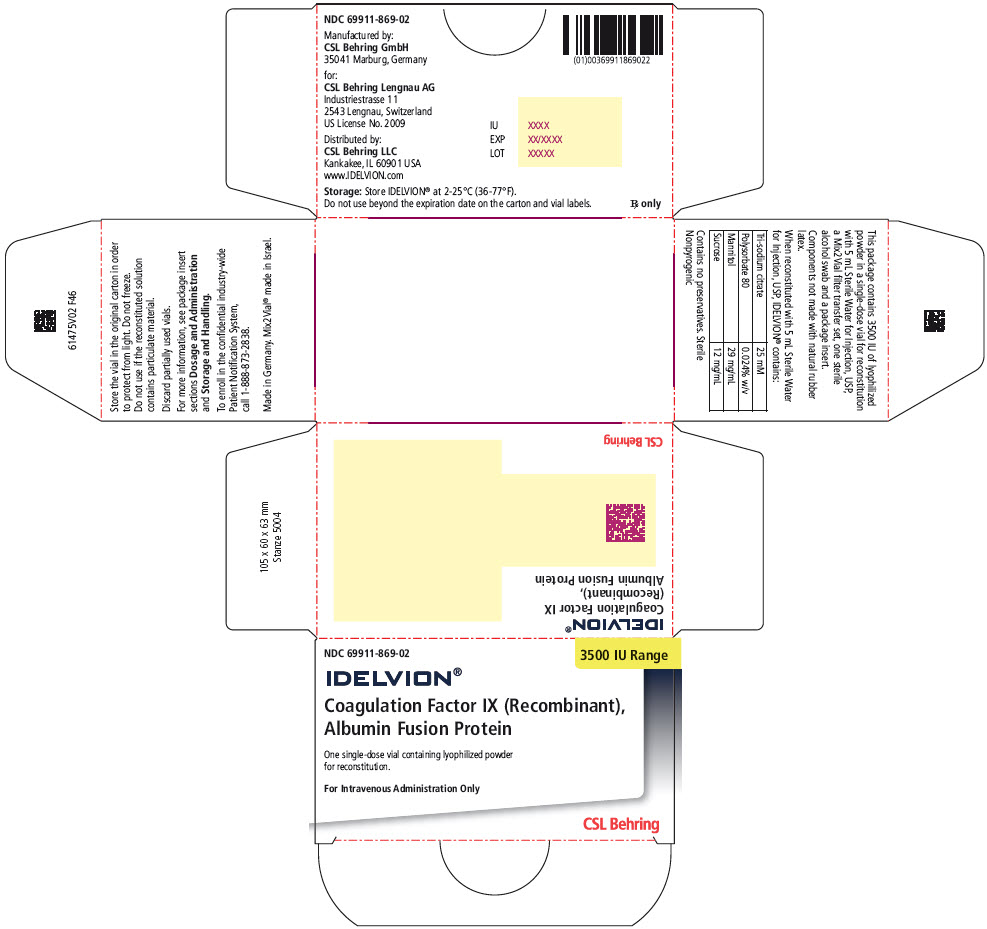 DRUG LABEL: IDELVION
NDC: 69911-864 | Form: KIT | Route: INTRAVENOUS
Manufacturer: CSL Behring Lengnau AG
Category: other | Type: PLASMA DERIVATIVE
Date: 20230630

ACTIVE INGREDIENTS: ALBUTREPENONACOG ALFA 250 [iU]/2.5 mL
INACTIVE INGREDIENTS: Sodium Citrate, Unspecified Form; Polysorbate 80; Mannitol; Sucrose; Water 2.5 mL/2.5 mL

HIGHLIGHTS OF PRESCRIBING INFORMATION

These highlights do not include all the information needed to use IDELVION® safely and effectively. See full prescribing information for IDELVION.
IDELVION [Coagulation Factor IX (Recombinant), Albumin Fusion Protein]
Lyophilized Powder for Solution for Intravenous Injection
Initial U.S. Approval: 2016

1 INDICATIONS AND USAGE

IDELVION, Coagulation Factor IX (Recombinant), Albumin Fusion Protein (rIX-FP), a recombinant DNA-derived coagulation Factor IX concentrate, is indicated in children and adults with Hemophilia B (congenital Factor IX deficiency) for:

- On-demand treatment and control of bleeding episodes
- Perioperative management of bleeding
- Routine prophylaxis to reduce the frequency of bleeding episodes

Limitations of Use:

IDELVION is not indicated for immune tolerance induction in patients with Hemophilia B. (1)

2 DOSAGE AND ADMINISTRATION

For intravenous use after reconstitution only.

- Each single-dose vial of IDELVION is labeled with the actual Factor IX potency in international units (IU). (2.1)
- One IU of IDELVION per kg body weight is expected to increase the circulating activity of Factor IX as follows:
  - Adolescents and adults: 1.3 IU/dL per IU/kg (2.1)
  - Pediatrics (<12 years): 1 IU/dL per IU/kg (2.1)
- Administer intravenously. Do not exceed infusion rate of 10 mL per minute. (2.3)

On-demand treatment and control of bleeding episodes and perioperative management:

- Dosage and duration of treatment with IDELVION depends on the severity of the Factor IX deficiency, the location and extent of bleeding, and the patient's clinical condition, age and recovery of Factor IX. (2.1)
- Determine the initial dose using the following formula:
  Required Dose (IU) = Body Weight (kg) × Desired Factor IX rise (% of normal or IU/dL) × (reciprocal of recovery (IU/kg per IU/dL)) (2.1)
- Adjust dose based on the patient's clinical condition and response. (2.1)

Routine prophylaxis:

- Patients ≥12 years of age: 25-40 IU/kg body weight every 7 days. Patients who are well-controlled on this regimen may be switched to a 14-day interval at 50-75 IU/kg body weight. (2.1)
- Patients <12 years of age: 40-55 IU/kg body weight every 7 days. (2.1)

3 DOSAGE FORMS AND STRENGTHS

IDELVION is available as a lyophilized powder in single-dose vials containing nominally 250, 500, 1000, 2000, or 3500 IU. (3)

4 CONTRAINDICATIONS

Do not use in patients who have had life-threatening hypersensitivity reactions to IDELVION or its components, including hamster proteins. (4)

5 WARNINGS AND PRECAUTIONS

- Hypersensitivity have been reported. Should symptoms of hypersensitivity reactions including anaphylaxis occur, discontinue IDELVION and administer appropriate treatment. (5.1)
- The formation of neutralizing antibodies (inhibitors) to Factor IX has been reported with IDELVION. If expected Factor IX plasma recovery in patient plasma is not attained, or if bleeding is not controlled with an appropriate dose, perform an assay that measures Factor IX inhibitor concentration. (5.2, 5.5)
- Thromboembolism (e.g., pulmonary embolism, venous thrombosis, and arterial thrombosis) may occur when using Factor IX-containing products. (5.3)
- Nephrotic syndrome has been reported following immune tolerance induction with Factor IX-containing products in hemophilia B patients with Factor IX inhibitors and a history of allergic reactions to Factor IX. (5.4)
- Factor IX activity assay results may vary with the type of activated partial thromboplastin time reagent used. (5.5)

6 ADVERSE REACTIONS

The most common adverse reactions (incidence ≥1%) reported in clinical trials were headache, dizziness, hypersensitivity and rash. (6)

To report SUSPECTED ADVERSE REACTIONS, contact CSL Behring Pharmacovigilance Department at 1-866-915-6958 or FDA at 1-800-FDA-1088 or www.fda.gov/medwatch.

8 USE IN SPECIFIC POPULATIONS

Pediatric: Higher dose per kilogram body weight or more frequent dosing may be needed. (8.4)

FULL PRESCRIBING INFORMATION

1 INDICATIONS AND USAGE

IDELVION®, Coagulation Factor IX (Recombinant), Albumin Fusion Protein (rIX-FP), a recombinant DNA-derived coagulation Factor IX concentrate, is indicated in children and adults with Hemophilia B (congenital Factor IX deficiency) for:

- On-demand treatment and control of bleeding episodes
- Perioperative management of bleeding
- Routine prophylaxis to reduce the frequency of bleeding episodes

Limitations of Use:

IDELVION is not indicated for immune tolerance induction in patients with Hemophilia B.

2 DOSAGE AND ADMINISTRATION

For intravenous use after reconstitution only.

2.1 Dosage

- Each single-dose vial of IDELVION contains the recombinant Factor IX potency in international units (IU) that is stated on the carton and vial label.
- Dosage and duration of treatment with IDELVION depends on the severity of Factor IX deficiency, the location and extent of bleeding, and the patient's clinical condition, age and recovery of Factor IX.
- The calculation of the required dose of IDELVION is based on the empirical finding that one IU of IDELVION per kg body weight is expected to increase the circulating level of Factor IX by 1.3 IU/dL in patients ≥12 years of age and by 1 IU/dL in patients <12 years of age. The required dose of IDELVION for treatment of bleeding episodes is determined using the following formula:
  Required Units (IU) = Body Weight (kg) × Desired Factor IX rise (% of normal or IU/dL) × (reciprocal of recovery (IU/kg per IU/dL))
  OR
  Increase in Factor IX IU/dL (or % of normal) = Dose (IU) × Recovery (IU/dL per IU/kg)/body weight (kg)
- Adjust the dose based on the individual patient's clinical condition and response.

On-demand Treatment and Control of Bleeding Episodes

A guide for dosing IDELVION for the on-demand treatment and control of bleeding episodes is provided in Table 1. Dosing should aim at maintaining a plasma Factor IX activity level at or above the plasma levels (in % of normal or IU/dL) outlined in Table 1.

Table 1. Dosing for On-demand Treatment and Control of Bleeding Episodes
Type of Bleeding Episode | Circulating Factor IX Activity Required [% or (IU/dL)] | Frequency of Dosing (hours) | Duration of Therapy (days) [Adapted from the WFH Guidelines for the Management of Hemophilia.]
Minor or Moderate Uncomplicated hemarthrosis, muscle bleeding (except iliopsoas) or oral bleeding | 30-60 | 48-72 | At least 1 day, until bleeding stops and healing is achieved. Single dose should be sufficient for majority of bleeds.
Major Life or limb threatening hemorrhage, deep muscle bleeding, including iliopsoas, intracranial, retropharyngeal | 60-100 | 48-72 | 7-14 days, until bleeding stops and healing is achieved. Maintenance dose weekly.

Perioperative Management of Bleeding

A guide for dosing IDELVION for perioperative management of bleeding is provided in Table 2.

Table 2. Dosing for Perioperative Management of Bleeding
Type of Surgery | Circulating Factor IX Activity Required [% or (IU/dL)] | Frequency of Dosing (hours) | Duration of Therapy (days) [Adapted from the WFH Guidelines for the Management of Hemophilia.]
Minor (including uncomplicated tooth extraction) | 50-80 | 48-72 | At least 1 day, or until healing is achieved. Single dose should be sufficient for a majority of minor surgeries.
Major (including intracranial, pharyngeal, retropharyngeal, retroperitoneal) | 60-100 (initial level) | 48-72 | 7-14 days, or until bleeding stops and healing is achieved. Repeat dose every 48-72 hours for the first week or until healing is achieved. Maintenance dose 1-2 times per week.

Routine Prophylaxis

For patients ≥12 years of age, the recommended dose is 25-40 IU IDELVION per kg body weight every 7 days. Patients who are well-controlled on a 7-day regimen may be switched to a 14-day interval at 50-75 IU IDELVION per kg body weight [see Clinical Studies (14)].

For patients <12 years of age, the recommended dose is 40-55 IU IDELVION per kg body weight every 7 days.

- A regimen may be further individually adjusted to less or more frequent dosing in adults.

2.2 Preparation and Reconstitution

The procedures below are provided as general guidelines for the preparation and reconstitution of IDELVION.

- Always work on a clean surface and wash your hands before performing the following procedures.
- Use aseptic technique during the reconstitution procedure.
- Reconstitute IDELVION using the diluent (Sterile Water for Injection) and transfer device (Mix2Vial) provided in the kit.
- To administer, you will also need a syringe and suitable needle (not provided).
- Ensure the vials of IDELVION and the Sterile Water for Injection are at room temperature before mixing.
- The reconstitution is performed as described below.

IDELVION Reconstitution Instructions

1. Place the IDELVION vial, diluent vial, and Mix2Vial® transfer set on a flat surface.
2. Remove flip caps from the IDELVION and Sterile Water for Injection (diluent) vials.
3. Wipe the stoppers with the sterile alcohol swab provided and allow to dry prior to opening the Mix2Vial transfer set package.
4. Open the Mix2Vial transfer set package by peeling away the lid (Fig. 1). Do not remove the device from the package.
  Fig. 1
5. Place the diluent vial on a flat surface and hold the vial tightly. Grip the Mix2Vial transfer set together with the clear package and push the plastic spike at the blue end of the Mix2Vial transfer set firmly through the center of the stopper of the diluent vial (Fig. 2).
  Fig. 2
6. Carefully remove the clear package from the Mix2Vial transfer set. Do not remove the Mix2Vial transfer set or touch the exposed end of the device (Fig. 3).
  Fig. 3
7. With the IDELVION vial placed firmly on a flat surface, invert the diluent vial with the Mix2Vial transfer set attached and push the plastic spike of the transparent adapter firmly through the center of the stopper of the IDELVION vial (Fig. 4). The diluent will automatically transfer into the IDELVION vial.
  Fig. 4
8. With the diluent and IDELVION vial still attached to the Mix2Vial transfer set, gently swirl the IDELVION vial to ensure that the powder is fully dissolved (Fig. 5). Do not shake the vial.
  Fig. 5
9. With one hand, grasp the IDELVION side of the Mix2Vial transfer set and with the other hand grasp the blue diluent-side of the Mix2Vial transfer set, and unscrew the set into two pieces (Fig. 6).
  Fig. 6
10. Draw air into an empty, sterile syringe. While the IDELVION vial is upright, screw the syringe to the Mix2Vial transfer set. Inject air into the IDELVION vial.
11. While keeping the syringe plunger pressed, invert the system upside down and draw the concentrate into the syringe by pulling the plunger back slowly (Fig. 7).
  Fig. 7
12. Disconnect the filled syringe by unscrewing it from the Mix2Vial transfer set (Fig. 8). The reconstituted solution should be a clear or yellow to colorless solution. Do not use if particulate matter or discoloration is observed.
  Fig. 8
13. Use immediately or within 4 hours of reconstitution. Store reconstituted solution at room temperature. Do not refrigerate.
14. If the dose requires more than one vial, use a separate, unused Mix2Vial transfer set and Sterile Water for Injection (diluent) vial for each product vial. Repeat steps 10-12 to pool the contents of the vials into one syringe.

2.3 Administration

For intravenous injection only.

- Do not mix or administer IDELVION in the same tubing or container with other medicinal products.
- Visually inspect the final solution for particulate matter and discoloration prior to administration, and whenever solution and container permit. Do not use if particulate matter or discoloration is observed.
- Attach the syringe containing the reconstituted IDELVION solution to a sterile infusion set and administer by intravenous injection. Adapt the infusion rate to the comfort level of each patient, not exceeding 10 mL per minute.
- Administer IDELVION at room temperature and within 4 hours of reconstitution. Discard any unused product.

3 DOSAGE FORMS AND STRENGTHS

IDELVION is a pale yellow to white lyophilized powder supplied in single-dose vials containing nominally 250, 500, 1000, 2000, or 3500 IU of Factor IX potency. The actual factor IX potency is labeled on each vial and carton.

4 CONTRAINDICATIONS

IDELVION is contraindicated in patients who have had life-threatening hypersensitivity reactions to IDELVION, or its components, including hamster proteins [see Warnings and Precautions (5.1)].

5 WARNINGS AND PRECAUTIONS

5.1 Hypersensitivity Reactions

Hypersensitivity reactions have occurred. Early signs of hypersensitivity reactions, which can progress to anaphylaxis include angioedema, chest tightness, hypotension, generalized urticaria, wheezing, and dyspnea. If symptoms of hypersensitivity or anaphylaxis occur, immediately discontinue administration and initiate appropriate treatment.

IDELVION contains trace amounts of Chinese hamster ovary (CHO) proteins. Patients treated with this product may develop hypersensitivity to these non-human mammalian proteins.

5.2 Neutralizing Antibodies

The formation of neutralizing antibodies (inhibitors) to Factor IX has been reported with IDELVION [see Adverse Reactions (6.3)]. Monitor all patients treated with IDELVION for the development of neutralizing antibodies (inhibitors) by appropriate clinical observations or laboratory tests. Perform an assay that measures Factor IX inhibitor concentration if expected plasma Factor IX activity levels are not attained, or if the bleeding is not controlled with an appropriate dose.

Patients with Factor IX inhibitors are at an increased risk of severe hypersensitivity reactions or anaphylaxis if re-exposed to Factor IX. Evaluate patients experiencing allergic reactions for the presence of an inhibitor and closely monitor patients with inhibitors for signs and symptoms of acute hypersensitivity reactions, particularly during early phases of exposure to the product [see Warnings and Precautions (5.1)].

5.3 Thromboembolic Complications

Thromboembolism (e.g., pulmonary embolism, venous thrombosis, and arterial thrombosis) may occur when using Factor IX-containing products. Because of the potential risk for thromboembolism with the use of Factor IX products, monitor for early signs of thromboembolism and consumptive coagulopathy when administering IDELVION to patients with liver disease, fibrinolysis, perioperative status, or risk factors for thromboembolic events or disseminated intravascular coagulation.

5.4 Nephrotic Syndrome

Nephrotic syndrome has been reported following attempted immune tolerance induction in hemophilia B patients with Factor IX inhibitors and a history of allergic reactions. The safety and efficacy of using IDELVION for immune tolerance induction have not been established.

5.5 Monitoring Laboratory Tests

- Monitor Factor IX plasma levels by a one-stage clotting assay to confirm that adequate Factor IX levels have been achieved and maintained [see Dosage and Administration (2.1)]. Factor IX activity assay results may vary with the type of activated partial thromboplastin time (aPTT) reagent used in the assay system.^1 For example, kaolin-based aPTT reagents along with other reagents designed to exhibit low responsiveness to lupus anticoagulant^2 have been shown to result in approximately 50% lower than expected recovery based on labeled potency.
- Consistent with similar findings for other recombinant Factor IX products, overestimation of Factor IX activity in spiked samples of IDELVION (mean overestimation 32%) occurred at low Factor IX levels with commonly used aPTT reagents.^3
- Monitor patients for the development of inhibitors if expected Factor IX activity plasma levels are not attained, or if bleeding is not controlled with the recommended dose of IDELVION. Assays used to determine if a Factor IX inhibitor is present should be titered in Bethesda Units (BUs).

6 ADVERSE REACTIONS

The most common adverse reactions (incidence ≥1%) reported in clinical trials were headache, dizziness, hypersensitivity and rash.

6.1 Clinical Trials Experience

Because clinical trials are conducted under widely varying conditions, adverse reaction rates observed in the clinical trials of a drug cannot be directly compared to rates in clinical trials of another drug and may not reflect the rates observed in clinical practice.

In five multicenter, prospective, open-label clinical trials with IDELVION, 114 previously treated patients (PTPs; exposed to a Factor IX-containing product for ≥100 exposure days (EDs)) received at least one infusion of IDELVION as part of on-demand treatment of bleeding episodes, perioperative management of major and minor surgical, dental, or other invasive procedures, routine prophylaxis, or pharmacokinetic evaluation. Twenty-seven children were <12 years of age, 9 adolescents were 12 to <18 years of age, and 78 adults were ≥18 to ≤65 years of age. A total of 16,326 injections were administered over a median of 1,543.5 days (range: 25 to 2,565 days).

Adverse reactions that occurred in >0.5% of subjects are listed in Table 3.

Table 3. Summary of Adverse Reactions in Previously Treated Patients
MedDRA Standard System Organ Class | Adverse Reaction | Number of subjects n (%), (N=114)
Nervous system disorders | Headache | 2 (1.8)
 | Dizziness | 2 (1.8)
Immune system disorders | Hypersensitivity | 1 (0.9)
Skin and subcutaneous tissue disorders | Rash | 1 (0.9)
 | Eczema | 1 (0.9)

Safety of IDELVION was also evaluated in a completed study with 12 previously untreated patients (PUPs). The median number of EDs was 50 (range: 22 to 146) per subject, a total of 8 subjects achieved at least 50 EDs, of whom 3 subjects achieved ≥100 EDs.

Adverse drug reactions were reported in 2 of 12 subjects treated with IDELVION. One subject (8.3%) in the PUP study developed a high titer of factor IX inhibitors (peak titer 188 BU/mL) and the same subject (8.3%) developed hypersensitivity. One additional subject (8.3%) in the PUP study developed rash.

6.2 Immunogenicity

All subjects were monitored for inhibitory and binding antibodies to rIX-FP (specifically rFIX, pdFIX and albumin), and binding antibodies to CHO host cell proteins at the following time points: at screening, at 2-4 weeks, 12 weeks following the first infusion of IDELVION, every 3 months thereafter (every 6 months for binding antibodies in children). No subjects developed non-neutralizing antibodies against factor IX, or antibodies to albumin and CHO protein at any of the time points following infusion of IDELVION. One case of inhibitor development to Factor IX was reported in the clinical study which evaluated previously untreated patients. No antibodies to Factor IX have been observed in IDELVION clinical trials which enrolled previously treated patients.

The detection of antibody formation is highly dependent on the sensitivity and specificity of the assay. Additionally, the observed incidence of antibody (including neutralizing antibody) positivity in an assay may be influenced by several factors including assay methodology, sample handling, timing of sample collection, concomitant medications, and underlying disease. For these reasons, it may be misleading to compare the incidence of antibodies to IDELVION in the studies described above with the incidence of antibodies in other studies or to other products.

6.3 Postmarketing Experience

The following adverse reaction has been identified during post-approval use of IDELVION. Because these reactions are reported voluntarily from a population of uncertain size, it is not always possible to reliably estimate their frequency or establish a causal relationship to drug exposure.

Blood and lymphatic system disorders: Factor IX inhibitor development

8 USE IN SPECIFIC POPULATIONS

8.1 Pregnancy

Risk Summary

There are no data with IDELVION use in pregnant women to inform on drug-associated risk. Animal reproduction studies have not been conducted using IDELVION. It is not known whether IDELVION can cause fetal harm or affect reproduction capacity when administered to a pregnant woman. In the U.S. general population, the estimated background risk of major birth defects and miscarriage in clinically recognized pregnancies is 2-4% and 15-20%, respectively.

8.2 Lactation

Risk Summary

There is no information regarding the excretion of IDELVION in human milk, the effect on the breastfed infant, or the effects on milk production. The developmental and health benefits of breastfeeding should be considered along with the mother's clinical need for IDELVION and any potential adverse effects on the breastfed infant from IDELVION or from the underlying maternal condition.

8.4 Pediatric Use

In clinical studies that included 34 previously treated patients (PTPs) <18 years old, the prophylactic administration with IDELVION every 7 days was successful in prevention of spontaneous bleeding episodes requiring treatment [see Clinical Studies (14)]. Of these, 7 subjects were ≥12 and <18 years old; 5 of these subjects switched to a 10- or 14-day prophylactic administration with IDELVION. There were no apparent differences in the safety profile in subjects <18 years as compared to adults [see Adverse Reactions (6.1)].

Compared to adults, incremental rIX-FP recovery appeared to be slightly lower and body weight-adjusted clearance appeared to be higher. Children may have higher Factor IX body weight-adjusted clearance, shorter half-life, and lower recovery. Higher dose per kilogram body weight or more frequent dosing may be needed in these patients [see Dosage and Administration (2.1) and Clinical Pharmacology (12.3)].

8.5 Geriatric Use

Clinical studies of IDELVION did not include subjects over 65 years to determine whether or not they respond differently from younger subjects.

11 DESCRIPTION

IDELVION, Coagulation Factor IX (Recombinant), Albumin Fusion Protein (rIX-FP) is a sterile, non-pyrogenic, lyophilized powder to be reconstituted with sterile Water for Injection (sWFI) for intravenous administration. IDELVION is available in single-dose vials containing nominally 250, 500, 1000, 2000, or 3500 IU of Factor IX formulated with sodium citrate, polysorbate 80, mannitol and sucrose. The actual amount of Factor IX activity in IU is labeled on each vial. After reconstitution of the lyophilized powder, all dosage strengths yield a clear, yellow to colorless solution. IDELVION contains no preservatives.

The active ingredient in IDELVION, recombinant human coagulation Factor IX albumin fusion protein, is a purified protein produced by recombinant DNA technology. It is generated by the genetic fusion of recombinant albumin to recombinant coagulation Factor IX. The genetic fusion of the cDNA of human albumin to the cDNA of human coagulation Factor IX enables the gene product to be expressed as a single recombinant protein designated as rIX-FP. The Factor IX portion of IDELVION is identical to the Thr148 allelic form of human plasma-derived Factor IX. The cleavable linker between the Factor IX and albumin moieties is derived from the endogenous activation peptide in native Factor IX. rIX-FP remains intact in the circulation until Factor IX is activated, whereupon albumin is cleaved from Factor IX, releasing activated Factor IX (FIXa) when it is needed for coagulation.

IDELVION is manufactured without the addition of proteins derived from human or animal source materials. IDELVION is a glycoprotein consisting of 1018 amino acids secreted by a genetically engineered Chinese hamster ovary (CHO) cell line. The CHO cell line secretes rIX-FP into a defined cell culture medium and the rIX-FP protein is purified by a process that does not require the use of a monoclonal antibody reagent. The manufacturing process incorporates three validated virus clearance steps, including virus inactivation by solvent/detergent treatment and virus removal by filtration.

The potency expressed in International Units is determined using an in vitro aPTT-based one-stage clotting assay against CSL Behring's manufacturing reference standard. This internal potency standard has been calibrated against the World Health Organization (WHO) International Standard for Factor IX concentrate by a one-stage clotting assay using synthetic silica and synthetic phospholipid-based reagents.

12 CLINICAL PHARMACOLOGY

12.1 Mechanism of Action

IDELVION is a recombinant protein that temporarily replaces the missing coagulation Factor IX needed for effective hemostasis. IDELVION is comprised of genetically fused recombinant coagulation Factor IX and recombinant albumin. Fusion with recombinant albumin extends the half-life of Factor IX [see Description (11) and Clinical Pharmacology (12.3)].

12.2 Pharmacodynamics

The administration of IDELVION increases plasma levels of Factor IX and can temporarily correct the coagulation defect in patients.

12.3 Pharmacokinetics

Adults ≥18 years

The pharmacokinetic (PK) profiles of IDELVION were evaluated following intravenous injections of single doses of 25, 50 or 75 IU/kg. The PK parameters were based on plasma Factor IX activity measured by the one-stage clotting assay. Blood samples for PK analysis were collected prior to dosing and up to 336 hours (14 days) after dosing.

Table 4 provides the pharmacokinetic parameters following a single 25 IU/kg, 50 IU/kg, or 75 IU/kg dose of IDELVION.

Table 4. Pharmacokinetic Parameters (Arithmetic Mean, CV%) Following a Single 25 IU/kg, 50 IU/kg, or 75 IU/kg Dose of IDELVION
PK Parameters | rIX-FP 25 (IU/kg) (N=7) | rIX-FP 50 (IU/kg) (N=47) | rIX-FP 75 (IU/kg) (N=8)
IR (IU/dL)/(IU/kg) | 1.65 (11) | 1.30 (24) | 1.08 (20)
Cmax (IU/dL) | 41.1 (13) | 66.6 (27) | 82.0 (20)
AUC0-inf (h*IU/dL) | 4658 (36) | 7482 (28) | 9345 (20)
t1/2 (hours) | 118 (38) | 104 (25) | 104 (18)
MRT (hours) | 153 (24) | 143 (23) | 145 (14)
CL (mL/h/kg) | 0.57 (31) | 0.73 (27) | 0.84 (20)
Vss (dL/kg) | 0.86 (32) | 1.02 (28) | 1.20 (23)
Time to 1% Factor IX Activity (days) [= Estimated time to mean Factor IX activity maintained above the pre-specified percent (%)] | 22 (25) | 23 (19) | 25 (13)
Time to 3% Factor IX Activity (days) | 14 (19) | 17 (19) | 18 (13)
Time to 5% Factor IX Activity (days) | 10 (25) | 13 (20) | 15 (13)
IR = incremental recovery recorded 30 minutes after injection; AUC = area under the Factor IX activity time curve; t1/2 = half-life; MRT = mean residence time; CL = body weight adjusted clearance; Vss = body weight adjusted volume of distribution at steady state.

IDELVION PK parameters following single or repeat dosing for up to 30 weeks were similar.

Subjects <18 years

Pharmacokinetic parameters of IDELVION were evaluated in 5 adolescents (12 to <18 years of age) and 27 children (0 to <12 years of age) in open-label, multi-center studies following a 50 IU/kg intravenous injection of IDELVION. The PK samples were collected prior to dosing and at multiple time points up to 336 hours (14 days) after dosing.

Table 5 summarizes the PK parameters calculated from the pediatric data of 32 subjects, 0 to <18 years of age. The parameters estimated were based on the plasma Factor IX activity over time profile. Compared to adults, incremental recovery is lower (15% to 27%) and body weight-adjusted clearance is higher (45% to 62%) in children.

Table 5. Pharmacokinetic Parameters (Arithmetic Mean, CV%) of IDELVION Following a Single 50 IU/kg Dose
PK Parameters | 0 to <6 years (N=12) | 6 to <12 years (N=15) | 12 to <18 years (N=5)
IR (IU/dL)/(IU/kg) | 0.95 (22) | 1.06 (23) | 1.11 (28)
Cmax (IU/dL) | 48.3 (19) | 52.9 (23) | 55.3 (28)
AUC0-inf (h*IU/dL) | 4583 (33) | 5123 (31) | 5347 (48)
t1/2 (hours) | 90 (13) | 93 (21) | 87 (36)
MRT (hours) | 123 (14) | 129 (19) | 119 (31)
CL (mL/h/kg) | 1.18 (28) | 1.06 (29) | 1.08 (39)
Vss (dL/kg) | 1.42 (24) | 1.32 (20) | 1.16 (14)
Time to 1% Factor IX Activity (days) [= Estimated time to mean Factor IX activity maintained above the pre-specified percent (%)] | 17 (29) | 20 (22) | 19 (37)
Time to 3% Factor IX Activity (days) | 12 (32) | 14 (22) | 13 (38)
Time to 5% Factor IX Activity (days) | 9 (32) | 11 (26) | 11 (38)
IR = incremental recovery recorded 30 minutes after injection; AUC = area under the Factor IX activity time curve; t1/2 = half-life; MRT = mean residence time; CL = body weight adjusted clearance; Vss = body weight adjusted volume of distribution at steady-state.

13 NONCLINICAL TOXICOLOGY

13.1 Carcinogenesis, Mutagenesis, Impairment of Fertility

Nonclinical studies evaluating the carcinogenic potential of IDELVION have not been conducted.

No macroscopic or microscopic pathologies in reproductive organs were observed in animals dosed every day for 28 days with 6.7 times the maximum recommended prophylactic clinical dose of 75 IU/kg IDELVION. No animal studies regarding impairment of fertility following IDELVION dosing were conducted.

14 CLINICAL STUDIES

The safety and efficacy of IDELVION were evaluated in a prospective, open-label, multicenter clinical study of 63 male previously treated patients (PTPs) with hemophilia B (≤2% endogenous Factor IX activity) who received at least one infusion of IDELVION as part of on-demand treatment and control of bleeding episodes, perioperative management of major and minor surgical, dental, or other invasive procedures, routine prophylaxis once every 7-, 10- or 14-day intervals, or pharmacokinetic evaluation. Subjects were aged 12 to 61 years; including 7 adolescent subjects aged 12 to 17. Subjects were treated for up to 27 months.

On-demand Treatment and Control of Bleeding Episodes

A total of 358 bleeding events were treated with IDELVION. Among them, 204 (57%) bleeding events were spontaneous, 140 (39%) events were traumatic and 14 (4%) events were unknown. In addition, a total of 267 (75%) episodes were joint bleeding events.

Overall treatment efficacy was assessed for each bleeding episode by the investigator based on a 4-point scale of excellent, good, moderate, or poor/no response. The efficacy of IDELVION for the on-demand treatment and control of bleeding episodes is summarized in Table 6.

Table 6. Efficacy [Excellent: Pain relief and/or unequivocal improvement in objective signs of bleeding and no additional infusion required in order to achieve hemostasis; Good: Definite pain relief and/or improvement in signs of bleeding at approximately 8 hours after the first infusion, but may require a second infusion; Moderate: Probable or slight beneficial effect, and requires more than two infusions to achieve hemostasis; Poor/no response: No improvement at all or condition worsens, additional hemostatic intervention is required. Responses evaluated at approximately 24 hours after treatment.] of IDELVION for the On-demand Treatment and Control of Bleeding Episodes
Number of Bleeding Episodes Requiring Treatment (n = 358)
Number of injections to treat bleeding episodes
1 injection, n (%) | 335 (94)
2 injections, n (%) | 18 (5)
>2 injections, n (%) | 5 (1.4)
Assessment of Efficacy
Excellent or Good, n (%) | 337 (94)
Moderate, n (%) | 9 (2.5)
Poor/no response, n (%) | 1 (0.3)

Perioperative Management of Bleeding

In the two effectiveness studies and the extension study, a total of 20 subjects (5-59 years of age) received IDELVION for perioperative management of 29 surgical procedures. Dose was individualized based on subject's PK and clinical response to treatment. These included orthopedic surgeries (n=14), a mastectomy with liposuction (n=1), a hemorrhoidectomy (n=2), rhinoplasty, submucosal resection and inferior turbinectomy (n=1), circumcision (n=3), tooth extractions (n=5), embolism of scrotal varicocele (n=1), excision of pigmented nevus (n=1) and endoscopic mucosal resection (n=1).

A single preoperative bolus was used in 97% (n=28) of surgeries. Hemostatic efficacy was rated as excellent or good for all surgeries at all time points for which hemostatic response was reported, except for one evaluation that was rated moderate at the 48-hour assessment. During the 14-day postoperative period, patients received between 0 and 11 infusions and FIX consumption was between 0 and 444.1 IU/kg. Six patients undergoing surgery were discharged from the surgical treatment site on the same day.

Routine Prophylaxis

Of the 63 subjects treated with IDELVION, twenty-three PTPs received IDELVION only for the treatment of bleeding episodes during the first 6 months of the study. Nineteen of these PTPs switched to once weekly prophylaxis with additional median duration of 10 months.

Based on the analysis of the 19 subjects treated with IDELVION for on-demand therapy and weekly prophylaxis, the median annualized spontaneous bleeding rate (AsBR) during prophylaxis treatment was 0.7 (range: 0 to 4.2), as compared to 15.4 (range: 2 to 39.5) during on-demand treatment. Based on the Poisson model, prophylaxis treatment with IDELVION resulted in a 93% reduction in the annualized spontaneous bleeding rate.

The median annualized bleeding rate (total ABR – spontaneous and traumatic) during prophylaxis treatment was 1.6; (range: 0 to 21.1), as compared to 19.2; (range: 2 to 46.1) during on demand treatment. Based on the Poisson model, prophylaxis treatment with IDELVION resulted in an 88% reduction in the annualized bleeding rate.

Table 7. Comparison of Annualized Bleeding Rates for Subjects Treated for On-demand Therapy and Weekly Prophylaxis
Bleeding Episode Etiology | On-demand (n=19) [Based on matched pairs design] | Weekly Prophylaxis (n=19) | Percent Reduction with Prophylaxis (n=19)
Spontaneous
Mean (SD) | 14.6 (8.42) | 0.9 (1.17) | 93.5 (8.03)
Median | 15.4 | 0.7 | 95.9
IQR | 8.0, 18.0 | 0, 1.6 | 89.0, 100
Range | 2.0, 39.5 | 0, 4.2 | 75.2, 100
Total [Total includes spontaneous and traumatic bleeds]
Mean (SD) | 20.8 (9.19) | 2.9 (4.79) | 88.0 (14.06)
Median | 19.2 | 1.6 | 90.9
IQR | 16.7, 25.8 | 0, 4.3 | 81.2, 100
Range | 2.0, 46.1 | 0, 21.1 | 54.3, 100
IQR=interquartile range, defined for 25th percentile and 75th percentile; SD=standard deviation; Subjects evaluable for efficacy are subjects who received at least one dose of on-demand treatment, and one dose of prophylaxis treatment.

Forty subjects received weekly routine prophylaxis. Thirty-seven subjects completed 6 months of once weekly prophylaxis. Of these, 21 subjects switched to a 14-day interval with 50-75 IU/kg of IDELVION with a median duration of 12.7 months. Prior to switching, these 21 subjects were well controlled with IDELVION (did not require dose adjustments or experience spontaneous bleeding 1 month prior to switch and were maintained on a prophylaxis dose of ≤40 IU/kg every 7 days).

The median AsBRs for the 21 subjects treated with weekly and 14-day prophylaxis were zero (range: 0 to 4.5) and zero (range: 0 to 7.3), respectively (summarized in Table 8). In addition, the median AsBRs for the 7 subjects treated with weekly and 10-day prophylaxis were zero (range: 0 to 0) and zero (range: 0 to 0.9), respectively.

Table 8. Comparison of Annualized Spontaneous Bleeding Rate (AsBR) by Prophylaxis Regimen for Subjects in the Clinical Trial
Bleeding Episode Etiology | Weekly Prophylaxis (n=21) [Based on a matched pairs design] | 14 day Prophylaxis (n=21)
Spontaneous
Mean (SD) | 0.28 (1.01) | 1.07 (2.1)
Median | 0 | 0
IQR | 0, 0 | 0, 1
Range | 0, 4.5 | 0, 7.3
IQR = interquartile range; SD = Standard deviation

Routine Prophylaxis and Control of Bleeding in PTPs <12 Years

Safety, efficacy, and pharmacokinetics of IDELVION have been evaluated in previously treated pediatric patients (PTPs) ranging from one (1) to <12 years of age. A total of 27 males, 12 patients <6 years of age and 15 patients between 6 to <12 years of age, received IDELVION for prophylaxis and control of bleeding episodes. All 27 subjects received weekly prophylaxis treatment with IDELVION for a mean time on study of 13.1 months (range: 9, 18 months).

The routine weekly regimen with rIX-FP was effective in the prophylaxis of bleeding episodes. The median (Q1, Q3) ABR (total bleeding episodes, including untreated) and annualized spontaneous bleeding rate (AsBR) during prophylaxis treatment in the efficacy population were 3.41 [1.18,7.44] and 0 [0, 1.34] bleeding episodes/subject/year, respectively. The mean ABR was 4.55 bleeding episodes/year/subject and the mean AsBR was 0.79 based on the total of both treated and untreated bleeding episodes. The target joints (defined as 3 or more spontaneous bleeds into a single joint within a consecutive 6-months period) reported in 3 subjects prior to study entry were resolved during the study. All subjects maintained a weekly routine prophylaxis regimen throughout.

Of the 106 bleeding episodes, the majority (94;89%) was treated with single injection, 103 (97%) were treated with 1-2 injections. Hemostatic efficacy at resolution of a bleed was rated excellent or good in 96% of all treated bleeding episodes.

15 REFERENCES

1. Wilmot HV, Hogwood J, Gray E. Recombinant factor IX: discrepancies between one-stage clotting and chromogenic assays. Haemophilia 2014, 1-7.
2. Fritsma GA, Dembitzer FR, Randhawa A, et al. Recommendations for Appropriate Activated Partial Thromboplastin Time Reagent Selection and Utilization. Am J Clin Pathol 2012;137:904-908.
3. Sommer JM, Buyue Y, Bardan S, Peters RT, Jiang H, Kamphaus G, Gray E, Pierce GF. Comparative field study: impact of laboratory assay variability on the assessment of recombinant factor IX Fc fusion protein (rFIXFc) activity. Thrombosis and Haemostasis 2014, 112(5):932-40.

16 HOW SUPPLIED/STORAGE AND HANDLING

IDELVION is supplied as a lyophilized powder in single-dose vials containing the labeled amount of Factor IX activity, expressed in international units (IU).

IDELVION is packaged with 2.5 mL (for reconstitution of 250, 500 or 1000 IU vials) or 5 mL (for reconstitution of 2000 or 3500 IU vials) of Sterile Water for Injection, USP, one Mix2Vial filter transfer set, and one sterile alcohol swab. Components are not made with natural rubber latex.

Table 9. How Supplied
Nominal Strength (International Units) | Fill Size Color Indicator | Kit NDC
250 | Orange | 69911-864-02
500 | Blue | 69911-865-02
1000 | Green | 69911-866-02
2000 | Purple | 69911-867-02
3500 | Yellow | 69911-869-02

Storage and Handling

- Store IDELVION in its package to protect from light.
- Store the IDELVION package in the refrigerator or at room temperature 2-25°C (36 to 77°F). Do not freeze.
- Do not use IDELVION or the Sterilized Water for Injection diluent beyond the expiration date printed on the carton and vial labels.

17 PATIENT COUNSELING INFORMATION

- Advise patients to read the FDA-approved patient labeling (Patient Information and Instructions for Use).
- Advise patients to report any adverse reactions or problems following IDELVION administration to their healthcare provider.
- Inform patients of the early signs and symptoms of hypersensitivity or allergic reactions (including hives, generalized urticaria, chest tightness, wheezing, and hypotension). Instruct patients to discontinue use of IDELVION and contact their healthcare provider and/or seek immediate emergency care if these symptoms occur [see Warnings and Precautions (5.1)].
- Advise patients to contact their healthcare provider or hemophilia treatment center for further treatment and/or assessment if they experience a lack of clinical response to Factor IX replacement therapy, as in some cases this may be a manifestation of an inhibitor [see Warnings and Precautions (5.2)].

Manufactured by:
CSL Behring GmbH
35041 Marburg, Germany

for:
CSL Behring Lengnau AG
Biotech Innovation Park
2543 Lengnau, Switzerland
US License No. 2009

Distributed by:
CSL Behring LLC
Kankakee, IL 60901 USA

IDELVION® is manufactured under a license by Novozymes Biopharma A/S, Bagsvaerd, Denmark.

Mix2Vial® is a registered trademark of West Pharma. Services IL, Ltd., a subsidiary of West Pharmaceutical Services, Inc.

FDA-Approved Patient Labeling

IDELVION® (eye del' vee on),
Coagulation Factor IX (Recombinant), Albumin Fusion Protein

This leaflet summarizes important information about IDELVION. Please read it carefully before using IDELVION. This information does not take the place of talking with your healthcare provider, and it does not include all of the important information about IDELVION. If you have any questions after reading this, ask your healthcare provider.

What is IDELVION?

IDELVION, Coagulation Factor IX (Recombinant), Albumin Fusion Protein is an injectable medicine used to replace clotting factor (Factor IX) that is missing in people with hemophilia B (also called congenital Factor IX deficiency or Christmas disease). Hemophilia B is an inherited bleeding disorder that prevents blood from clotting normally. IDELVION is used in children and adults with hemophilia B to control and prevent bleeding episodes. Your healthcare provider may give you IDELVION when you have surgery. IDELVION can reduce the number of bleeding episodes when used regularly (prophylaxis).

Who should not use IDELVION?

You should not use IDELVION if you:

- have had life-threatening hypersensitivity reactions to IDELVION
- are allergic to hamster proteins
- are allergic to any ingredients in IDELVION

Tell your healthcare provider if you have had an allergic reaction to any Factor IX product prior to using IDELVION.

Tell your healthcare provider if you are pregnant or breast-feeding because IDELVION may not be right for you.

What should I tell my healthcare provider before using IDELVION?

You should tell your healthcare provider if you:

- have or had any medical problems
- take any medicines, including prescription and non-prescription medicines, such as over-the-counter medicines, supplements, or herbal remedies
- have any allergies, including allergies to hamster proteins
- are breastfeeding. It is not known if IDELVION passes into your milk and if it can harm your baby.
- are pregnant or planning to become pregnant. It is not known if IDELVION may harm your unborn baby.
- have been told that you have inhibitors to Factor IX (because IDELVION may not work for you).

How should I administer IDELVION?

- IDELVION is given directly into the bloodstream.
- IDELVION should be administered as ordered by your healthcare provider.
- You should be trained on how to do injections by your healthcare provider or hemophilia treatment center. Many people with hemophilia B learn to inject IDELVION by themselves or with the help of a family member. See the step-by-step guide (Instructions for Use) provided at the end of this leaflet for directions on mixing and infusing IDELVION.
- Your healthcare provider will tell you how much IDELVION to use based on your weight, the severity of your hemophilia B, and where you are bleeding.
- You may need to have blood tests done after getting IDELVION to be sure that your blood level of Factor IX is high enough to clot your blood.
- Call your healthcare provider right away if your bleeding does not stop after taking IDELVION.

What are the possible side effects of IDELVION?

Allergic and hypersensitivity reactions have been reported with IDELVION. Call your healthcare provider right away and stop treatment if you get a rash or hives, itching, tightness of the chest or throat, difficulty breathing, light-headedness, dizziness, nausea, or decrease in blood pressure.

Your body can make antibodies, called inhibitors, against Factor IX which may stop IDELVION from working properly. Your healthcare provider may need to test your blood for inhibitors from time to time.

IDELVION may increase the risk of forming abnormal blood clots in your body, especially if you have risk factors for developing blood clots. Call your healthcare provider if you have chest pain, difficulty breathing, leg tenderness or swelling.

The most common side effects of IDELVION are headache and dizziness.

This is not the only side effect possible with IDELVION. To learn more, talk to your healthcare provider or pharmacist. Tell your healthcare provider about any side effect that bothers you or does not go away.

What are the IDELVION dosage strengths?

IDELVION comes in five different dosage strengths: 250, 500, 1000, 2000, or 3500 IU. The actual strength of IDELVION is printed on the carton and vial label. The labeling of the five dosage strengths are color-coded as provided in Table 1 below.

Table 1. IDELVION Dosage Strengths
Fill Size Color Indicator | Nominal Strength
Orange | 250 IU
Blue | 500 IU
Green | 1000 IU
Purple | 2000 IU
Yellow | 3500 IU

Always check the actual dosage strength printed on the label to make sure you are using the strength prescribed by your healthcare provider.

How should I store IDELVION?

- Store vial in original carton to protect from light.
- Store at 2-25°C (36-77°F). Do not freeze.
- Do not use IDELVION after the expiration date printed on the label.
- The reconstituted product (after mixing dry product with diluent) must be used within 4 hours and cannot be stored or refrigerated. Discard any IDELVION left in the vial at the end of your infusion.

What else should I know about IDELVION?

- Do not use IDELVION for a condition for which it is not prescribed.
- Do not share IDELVION with other people, even if they have the same symptoms that you have.

Instructions for Use

For intravenous use after reconstitution only.

Do not attempt to do an intravenous injection unless you have been taught how by your healthcare provider or hemophilia center.

Always follow the specific instructions given by your healthcare provider. The steps listed below are general guidelines for using IDELVION. If you are unsure of the instructions, call your healthcare provider before using IDELVION. Call your healthcare provider right away if bleeding is not controlled after using IDELVION. Your healthcare provider will prescribe the dose that you should take. You may need to have blood tests from time to time. Talk to your healthcare provider before traveling. Dispose of all unused solution, empty vial(s), and other used medical supplies in an appropriate medical waste container.

- Always work on a clean, flat surface and wash your hands before performing the mixing (reconstitution) procedures.
- Mix (reconstitute) IDELVION using the diluent (Sterile Water for Injection) and transfer device (Mix2Vial) provided in the kit.
- To give an injection, you will also need a syringe and suitable needle (not provided).
- If a package is opened or damaged, do not use and contact your healthcare provider.
- Do not use IDELVION beyond the expiration date on the vial label and carton.
- Look at the mixed (reconstituted) solution. Do not use IDELVION if the reconstituted solution is cloudy, contains any particles, or is discolored.
- Each vial of IDELVION is for single-dose only. Contains no preservatives. Discard partially used vials.
- Ensure the vials of IDELVION and the Sterile Water for Injection are at room temperature before mixing.
- Follow the reconstitution instructions as described below.

IDELVION Reconstitution Instructions

1. Place the IDELVION vial, diluent vial, and Mix2Vial® transfer set on a flat surface.
2. Remove flip caps from the IDELVION and Sterile Water for Injection (diluent) vials.
3. Wipe the stoppers with the sterile alcohol swab provided and allow to dry prior to opening the Mix2Vial transfer set package.
4. Open the Mix2Vial transfer set package by peeling away the lid (Fig. 1). Do not remove the device from the package.
  Fig. 1
5. Place the diluent vial on a flat surface and hold the vial tightly. Grip the Mix2Vial transfer set together with the clear package and push the plastic spike at the blue end of the Mix2Vial transfer set firmly through the center of the stopper of the diluent vial (Fig. 2).
  Fig. 2
6. Carefully remove the clear package from the Mix2Vial transfer set. Do not remove the Mix2Vial transfer set or touch the exposed end of the device (Fig. 3).
  Fig. 3
7. With the IDELVION vial placed firmly on a flat surface, invert the diluent vial with the Mix2Vial transfer set attached and push the plastic spike of the transparent adapter firmly through the center of the stopper of the IDELVION vial (Fig. 4). The diluent will automatically transfer into the IDELVION vial.
  Fig. 4
8. With the diluent and IDELVION vial still attached to the Mix2Vial transfer set, gently swirl the IDELVION vial to ensure that the powder is fully dissolved (Fig. 5). Do not shake the vial.
  Fig. 5
9. With one hand, grasp the IDELVION side of the Mix2Vial transfer set and with the other hand grasp the blue diluent-side of the Mix2Vial transfer set, and unscrew the set into two pieces (Fig. 6).
  Fig. 6
10. Draw air into an empty, sterile syringe. While the IDELVION vial is upright, screw the syringe to the Mix2Vial transfer set. Inject air into the IDELVION vial.
11. While keeping the syringe plunger pressed, invert the system upside down and draw the concentrate into the syringe by pulling the plunger back slowly (Fig. 7).
  Fig. 7
12. Disconnect the filled syringe by unscrewing it from the Mix2Vial transfer set (Fig. 8). The reconstituted solution should be a clear or yellow to colorless solution. Do not use if particulate matter or discoloration is observed.
  Fig. 8
13. Use immediately or within 4 hours of reconstitution. Keep solution at room temperature. Do not refrigerate after reconstitution.
14. If the dose requires more than one vial, use a separate, unused Mix2Vial transfer set and Sterile Water for Injection (diluent) vial for each product vial. Repeat steps 10-12 to pool the contents of the vials into one syringe.
15. Record treatment – Remove the peel-off portion of the label from each vial used and affix it to the patient's treatment diary/log book.

Administration (intravenous injection)

- Do not mix IDELVION in the same tubing or container with other medicinal products.
- Attach the syringe containing the reconstituted IDELVION solution to a sterile infusion set and give an injection as directed by your healthcare provider or hemophilia treatment center.
- Administer intravenously. Do not exceed infusion rate 10 mL per minute.

Resources at CSL Behring available to the patient:
For Adverse Reaction Reporting contact:
CSL Behring Pharmacovigilance Department at 1-866-915-6958

Contact CSL Behring to receive more product information:
Patient Support Hotline at 1-800-676-4266

For more information, visit www.IDELVION.com

Manufactured by:
CSL Behring GmbH
35041 Marburg, Germany

for:
CSL Behring Lengnau AG
Biotech Innovation Park
2543 Lengnau, Switzerland
US License No. 2009

Distributed by:
CSL Behring LLC
Kankakee, IL 60901 USA

IDELVION® is manufactured under a license by Novozymes Biopharma A/S, Bagsvaerd, Denmark.

Mix2Vial® is a registered trademark of West Pharma. Services IL, Ltd., a subsidiary of West Pharmaceutical Services, Inc.

Revised: 6/2023

PRINCIPAL DISPLAY PANEL - 250 IU Range Kit Carton

NDC 69911-864-02

250 IU Range

IDELVION®

Coagulation Factor IX (Recombinant),
Albumin Fusion Protein

One single-use vial containing lyophilized powder
for reconstitution.

For Intravenous Administration Only

CSL Behring

PRINCIPAL DISPLAY PANEL - 500 IU Range Kit Carton

NDC 69911-865-02

500 IU Range

IDELVION®

Coagulation Factor IX (Recombinant),
Albumin Fusion Protein

One single-use vial containing lyophilized powder
for reconstitution.

For Intravenous Administration Only

CSL Behring

PRINCIPAL DISPLAY PANEL - 1000 IU Range Kit Carton

NDC 69911-866-02

1000 IU Range

IDELVION®

Coagulation Factor IX (Recombinant),
Albumin Fusion Protein

One single-use vial containing lyophilized powder
for reconstitution.

For Intravenous Administration Only

CSL Behring

PRINCIPAL DISPLAY PANEL - 2000 IU Range Kit Carton

NDC 69911-867-02

2000 IU Range

IDELVION®

Coagulation Factor IX (Recombinant),
Albumin Fusion Protein

One single-use vial containing lyophilized powder
for reconstitution.

For Intravenous Administration Only

CSL Behring

PRINCIPAL DISPLAY PANEL - 3500 IU Range Kit Carton

NDC 69911-869-02

3500 IU Range

IDELVION®

Coagulation Factor IX (Recombinant),
Albumin Fusion Protein

One single-use vial containing lyophilized powder
for reconstitution.

For Intravenous Administration Only

CSL Behring